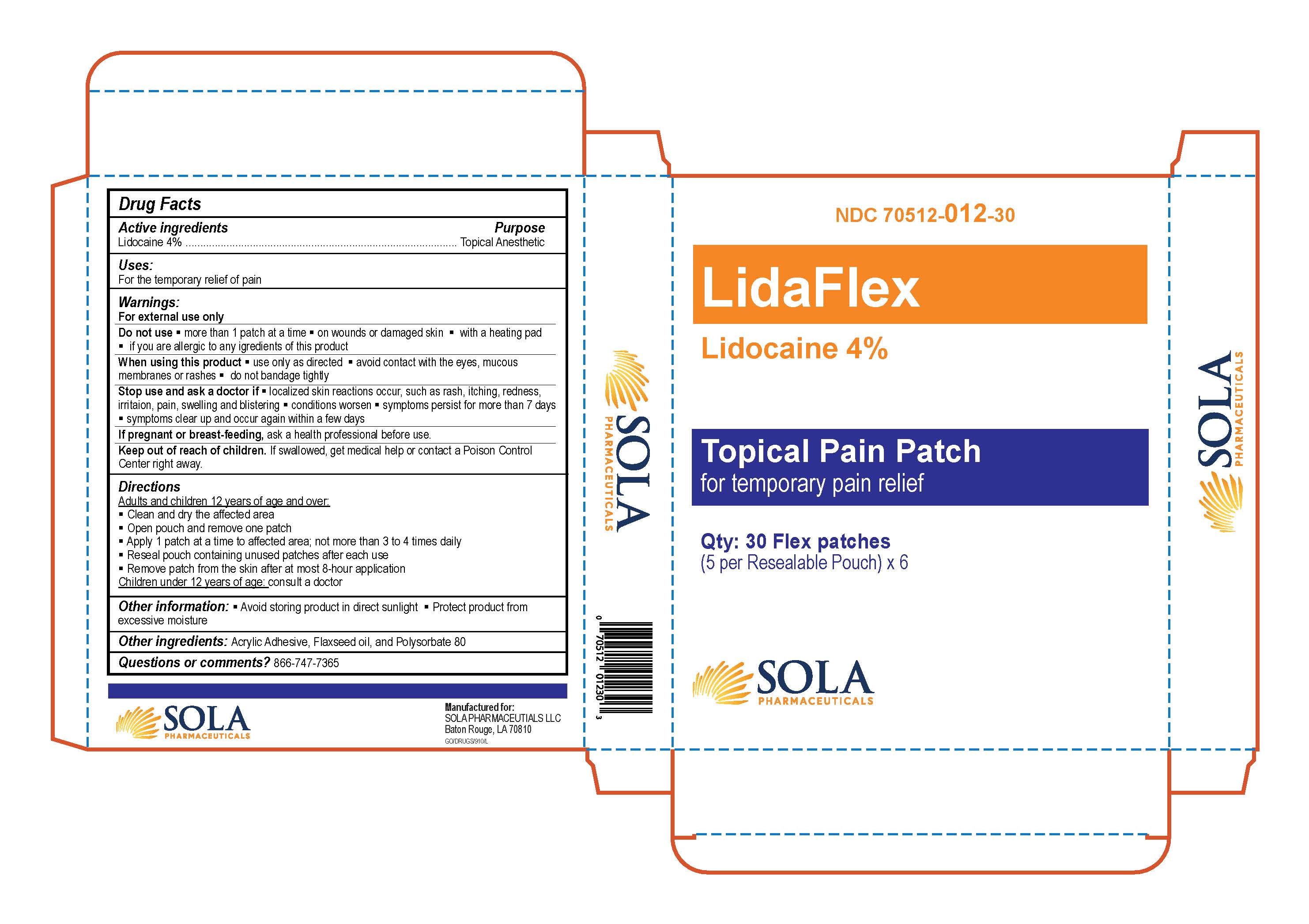 DRUG LABEL: Lidocaine 4% Patch
NDC: 70512-014 | Form: PATCH
Manufacturer: SOLA Pharmaceuticals
Category: otc | Type: HUMAN OTC DRUG LABEL
Date: 20251208

ACTIVE INGREDIENTS: LIDOCAINE 40 mg/1 g
INACTIVE INGREDIENTS: FLAX SEED; POLYSORBATE 80; ACRYLIC ACID

Lidocaine 4% Topical Patch

Active Ingredients

Lidocaine 4%

Purpose

Topical Anesthetic

Uses

For the temporary relief of pain

Warnings

For external use only

Do not use:

- More than 1 patch at a time
- On wounds or damaged skin
- With a heating pad
- If you are allergic to any ingredients of this product

When using this product:

- Use only as directed
- Avoid contact with the eyes, mucous membranes, or rashes
- Do not bandage tightly

Stop use and ask a doctor if:

- Localized skin reactions occur, such as rash, itching, redness, irritation, pain, swelling and blistering
- Conditions worsen
- Symptoms persist for more than 7 days
- Symptoms clear up and occur again within a few days

PREGNANCY OR BREAST FEEDING

If pregnant or breast-feeding, ask a health professional before use.

Keep out of reach of children. If swallowed, get medical help or contact a Poison Control Center right away.

Directions

Adults and children 12 years of age or over:

- Clean and dry the affected area
- Open pouch and remove one patch
- Apply 1 patch at a time to affected area; not more than 3 to 4 times daily
- Reseal pouch containing unused patches after each use
- Remove patch from the skin after at most 8-hour application

Children under 12 years of age:

- Consult a doctor

Other Information

- Avoid storing product in direct sunlight
- Protect product from excessive moisture

Other Ingredients

Acrylic Adhesive, Flaxseed oil, and Polysorbate 80

Questions or comments? 866-747-7365

Lidocaine 4% Patch

NDC 70512-014-30

Qty: 30 Flex Patches

(5 per resealable pouch) x 6

Manufactured for:

SOLA Pharmaceuticals

Baton Rouge, LA 70810